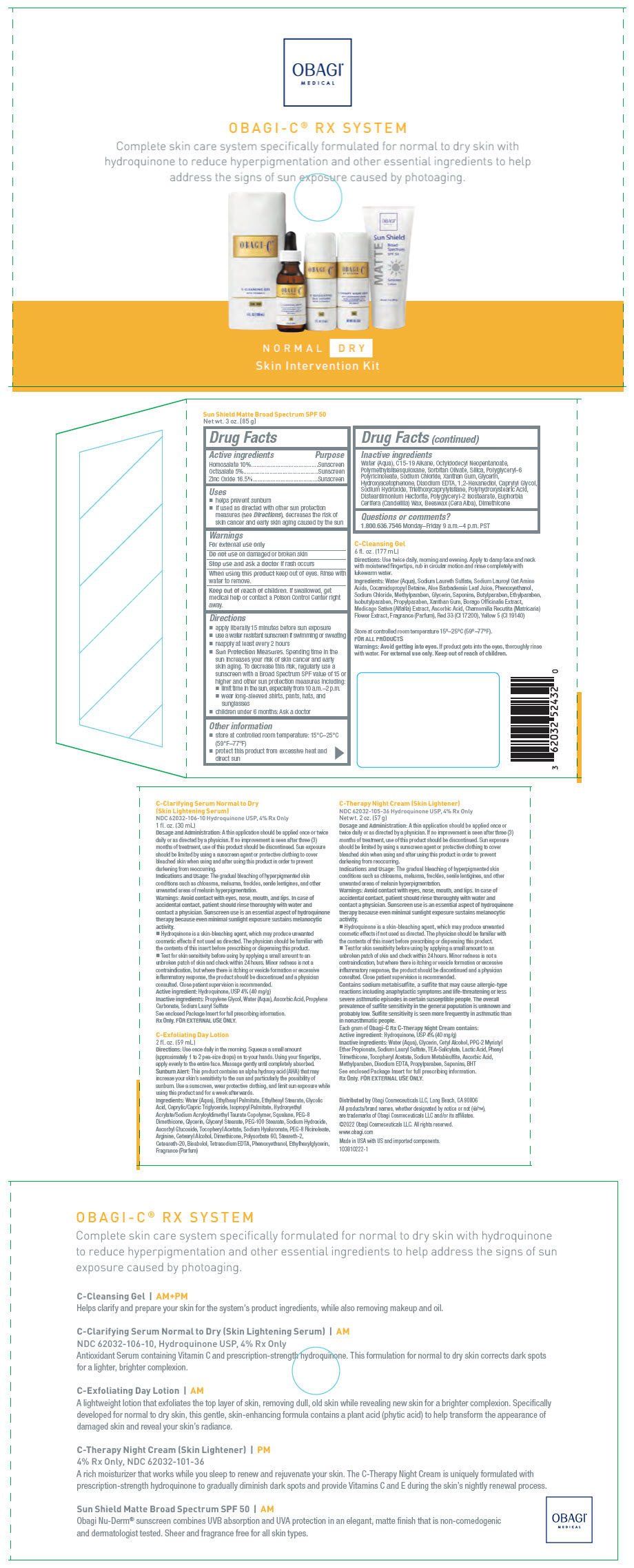 DRUG LABEL: Obagi-C C-Rx System Normal-Dry Skin Intervention
NDC: 62032-916 | Form: KIT | Route: TOPICAL
Manufacturer: Obagi Cosmeceuticals LLC
Category: otc | Type: HUMAN OTC DRUG LABEL
Date: 20260126

ACTIVE INGREDIENTS: HYDROQUINONE 40 mg/1 mL; HYDROQUINONE 40 mg/1 g; HOMOSALATE 100 mg/1 g; OCTISALATE 50 mg/1 g; ZINC OXIDE 165 mg/1 g
INACTIVE INGREDIENTS: PROPYLENE GLYCOL; WATER; ASCORBIC ACID; SODIUM LAURYL SULFATE; PROPYLENE CARBONATE; EDETATE DISODIUM; PPG-2 MYRISTYL ETHER PROPIONATE; TROLAMINE SALICYLATE; SODIUM LAURYL SULFATE; CETYL ALCOHOL; LACTIC ACID, UNSPECIFIED FORM; .ALPHA.-TOCOPHEROL ACETATE; ASCORBIC ACID; SODIUM METABISULFITE; METHYLPARABEN; PROPYLPARABEN; BUTYLATED HYDROXYTOLUENE; PHENYL TRIMETHICONE; GLYCERIN; WATER; WATER; GLYCERIN; HYDROXYACETOPHENONE; XANTHAN GUM; SODIUM CHLORIDE; SODIUM HYDROXIDE; OCTYLDODECYL NEOPENTANOATE; TRIETHOXYCAPRYLYLSILANE; C15-19 ALKANE; DISTEARDIMONIUM HECTORITE; SORBITAN OLIVATE; DIMETHICONE, UNSPECIFIED; 1,2-HEXANEDIOL; CAPRYLYL GLYCOL; EDETATE DISODIUM; CANDELILLA WAX; YELLOW WAX; POLYMETHYLSILSESQUIOXANE (4.5 MICRONS); SILICON DIOXIDE

Obagi-C® C-Rx System Normal-Dry Skin Intervention

Drug Facts

ACTIVE INGREDIENT

Active ingredients | Purpose
Homosalate 10% | Sunscreen
Octisalate 5% | Sunscreen
Zinc Oxide 16.5% | Sunscreen

Uses

- helps prevent sunburn
- If used as directed with other sun protection measures (see Directions), decreases the risk of skin cancer and early skin aging caused by the sun

Warnings

For external use only

Do not use on damaged or broken skin

Stop use and ask a doctor if rash occurs

When using this product keep out of eyes. Rinse with water to remove.

Keep out of reach of children. If swallowed, get medical help or contact a Poison Control Center right away.

Directions

- apply liberally 15 minutes before sun exposure
- use a water resistant sunscreen if swimming or sweating
- reapply at least every 2 hours
- Sun Protection Measures. Spending time in the sun increases your risk of skin cancer and early skin aging. To decrease this risk, regularly use a sunscreen with a Broad Spectrum SPF value of 15 or higher and other sun protection measures including:
  - limit time in the sun, especially from 10 a.m.–2 p.m.
  - wear long-sleeved shirts, pants, hats, and sunglasses
- children under 6 months: Ask a doctor

Other information

- store at controlled room temperature: 15°C–25°C (59°F–77°F)
- protect this product from excessive heat and direct sun

Inactive ingredients

Water (Aqua), C15-19 Alkane, Octyldodecyl Neopentanoate, Polymethylsilsesquioxane, Sorbitan Olivate, Silica, Polyglyceryl-6 Polyricinoleate, Sodium Chloride, Xanthan Gum, Glycerin, Hydroxyacetophenone, Disodium EDTA, 1,2-Hexanediol, Caprylyl Glycol, Sodium Hydroxide, Triethoxycaprylylsilane, Polyhydroxystearic Acid, Disteardimonium Hectorite, Polyglyceryl-2 Isostearate, Euphorbia Cerifera (Candelilla) Wax, Beeswax (Cera Alba), Dimethicone

Questions or comments?

1.800.636.7546 Monday–Friday 9 a.m.–4 p.m. PST

Distributed by Obagi Cosmeceuticals LLC, Long Beach, CA 90806

PRINCIPAL DISPLAY PANEL - Kit Carton

OBAGI®
MEDICAL

OBAGI-C® RX SYSTEM

Complete skin care system specifically formulated for normal to dry skin with
hydroquinone to reduce hyperpigmentation and other essential ingredients to help
address the signs of sun exposure caused by photoaging.

NORMAL DRY

Skin Intervention Kit